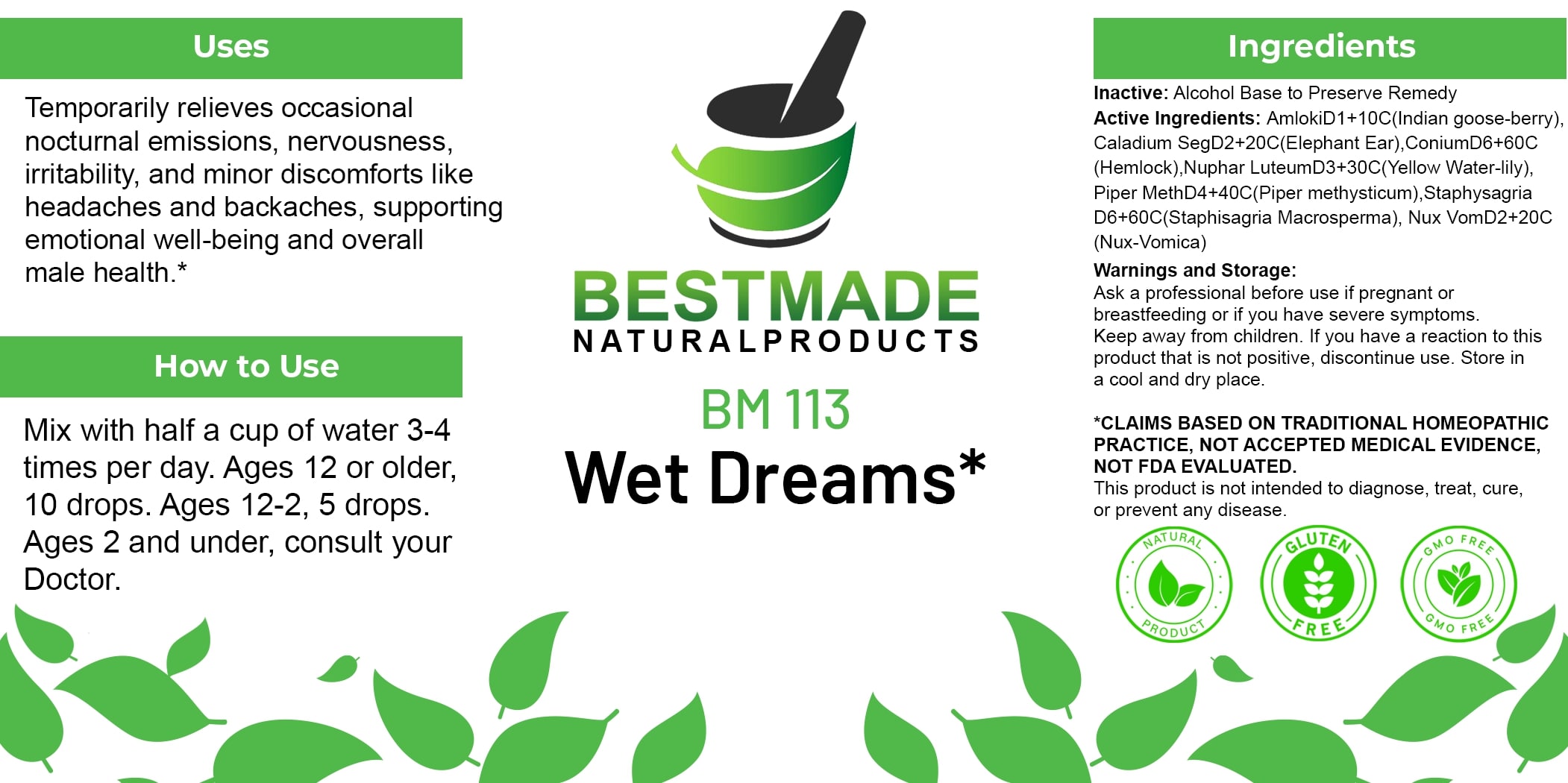 DRUG LABEL: Bestmade Natural Products BM113
NDC: 82969-2113 | Form: LIQUID
Manufacturer: Bestmade Natural Products
Category: homeopathic | Type: HUMAN OTC DRUG LABEL
Date: 20250207

ACTIVE INGREDIENTS: DIEFFENBACHIA SEGUINE 30 [hp_C]/30 [hp_C]; EMBLICA OFFICINALIS FRUIT 30 [hp_C]/30 [hp_C]; PIPER METHYSTICUM ROOT 30 [hp_C]/30 [hp_C]; CONIUM MACULATUM FLOWERING TOP 30 [hp_C]/30 [hp_C]; DELPHINIUM STAPHISAGRIA SEED 30 [hp_C]/30 [hp_C]; NUPHAR LUTEUM ROOT 30 [hp_C]/30 [hp_C]; STRYCHNOS NUX-VOMICA SEED 30 [hp_C]/30 [hp_C]
INACTIVE INGREDIENTS: ALCOHOL 30 [hp_C]/30 [hp_C]

BM113

DOSAGE AND ADMINISTRATION

How to Use

Mix with half a cup of water 3-4 times per day. Ages 12 or older, 10 drops. Ages 12-2, 5 drops. Ages 2 and under, consult your Doctor.

Inactive:

Alcohol Base to Preserve Product

Active Ingredients:

AmlokiD1+10C (Indian goose-berry Caladium SegD2+20C(Elephant Ear), ConiumD6+60C (Hemlock),Nuphar LuteumD3+30C(Yellow Water-lily) Piper MethD4+40C(Piper methysticum), Staphysagria D6+60C(Staphisagria Macrosperma), Nux VomD2+206 (Nux-Vomica)

Uses
Temporarily relieves occasional nocturnal emissions, nervousness. irritability, and minor discomforts like headaches and backaches, supporting emotional well-being and overall male health.*

Uses
Temporarily relieves occasional nocturnal emissions, nervousness. irritability, and minor discomforts like headaches and backaches, supporting emotional well-being and overall male health.*

KEEP OUT OF REACH OF CHILDREN

Warnings and Storage:

Ask a professional before use if pregnant or breastfeeding or if you have severe symptoms.

Keep away from children. If you have a reaction to this product that is not positive, discontinue use. Store in a cool and dry place

*CLAIMS BASED ON TRADITIONAL HOMEOPATHIC PRACTICE, NOT ACCEPTED MEDICAL EVIDENCE NOT FDA EVALUATED.
This product is not intended to diagnose, treat, cure, or prevent any disease.

Warnings and Storage:

Ask a professional before use if pregnant or breastfeeding or if you have severe symptoms.

Keep away from children. If you have a reaction to this product that is not positive, discontinue use. Store in a cool and dry place

*CLAIMS BASED ON TRADITIONAL HOMEOPATHIC PRACTICE, NOT ACCEPTED MEDICAL EVIDENCE NOT FDA EVALUATED.
This product is not intended to diagnose, treat, cure, or prevent any disease.

Entire package label